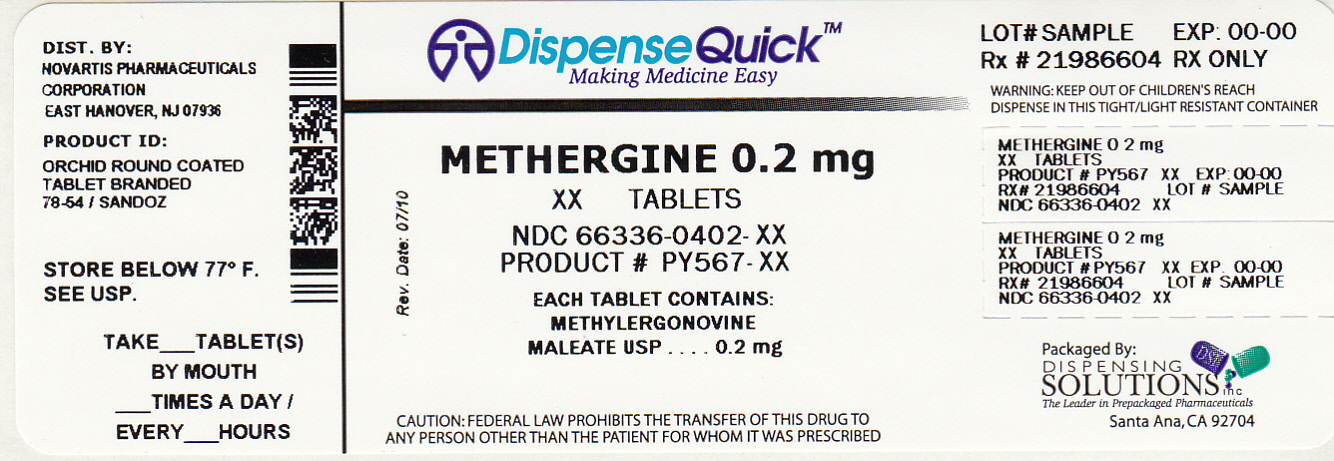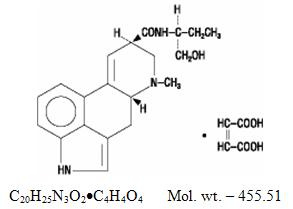 DRUG LABEL: Methergine
NDC: 66336-402 | Form: TABLET, COATED
Manufacturer: Dispensing Solutions, Inc.
Category: prescription | Type: HUMAN PRESCRIPTION DRUG LABEL
Date: 20110922

ACTIVE INGREDIENTS: METHYLERGONOVINE MALEATE 0.2 mg/1 1
INACTIVE INGREDIENTS: ACACIA; CARNAUBA WAX; D&C RED NO. 7; FD&C BLUE NO. 1; GELATIN; LACTOSE; MALEIC ACID; PROPYLPARABEN; POVIDONE; SODIUM BENZOATE; SODIUM HYDROXIDE; STARCH, CORN; STEARIC ACID; SUCROSE; TALC; TITANIUM DIOXIDE; METHYLPARABEN

Methergine

T2006-91

Methergine®

(methylergonovine maleate)

Tablets, USP

(methylergonovine maleate)

Injection, USP

Rx only

DESCRIPTION

Methergine® (methylergonovine maleate) is a semi-synthetic ergot alkaloid used for the prevention and control of postpartum hemorrhage.

Methergine is available in sterile ampuls of 1 mL, containing 0.2 mg methylergonovine maleate for intramuscular or intravenous injection and in tablets for oral ingestion containing 0.2 mg methylergonovine maleate.

Tablets

Active Ingredient: methylergonovine maleate, USP, 0.2 mg.

Inactive Ingredients: acacia, carnauba wax, D&C Red #7, FD&C Blue #1, gelatin special, lactose, maleic acid, mixed parabens, povidone, sodium benzoate, sodium hydroxide, starch, stearic acid, sucrose, talc, and titanium dioxide.

Ampuls, 1 mL, clear, colorless solution.

Active Ingredient: methylergonovine maleate, USP, 0.2 mg.

Inactive Ingredients: maleic acid, 0.10 mg; sodium chloride, 7.0 mg; water for injection, qs to 1 mL.

Chemically, methylergonovine maleate is designated as ergoline-8-carboxamide, 9,10-didehydro-N-[1-(hydroxymethyl)propyl]-6-methyl-, [8β(S)]-, (Z)-2-butenedioate (1:1) (salt).

Its structural formula is

CLINICAL PHARMACOLOGY

Methergine® (methylergonovine maleate) acts directly on the smooth muscle of the uterus and increases the tone, rate, and amplitude of rhythmic contractions. Thus, it induces a rapid and sustained tetanic uterotonic effect which shortens the third stage of labor and reduces blood loss. The onset of action after I.V. administration is immediate; after I.M. administration, 2-5 minutes, and after oral administration, 5-10 minutes.

Pharmacokinetic studies following an I.V. injection have shown that methylergonovine is rapidly distributed from plasma to peripheral tissues within 2-3 minutes or less. The bioavailability after oral administration was reported to be about 60% with no accumulation after repeated doses. During delivery, with intramuscular injection, bioavailability increased to 78%. Ergot alkaloids are mostly eliminated by hepatic metabolism and excretion, and the decrease in bioavailability following oral administration is probably a result of first-pass metabolism in the liver.

Bioavailability studies conducted in fasting healthy female volunteers have shown that oral absorption of a 0.2 mg methylergonovine tablet was fairly rapid with a mean peak plasma concentration of 3243 ± 1308 pg/mL observed at 1.12 ± 0.82 hours. For a 0.2 mg intramuscular injection, a mean peak plasma concentration of 5918 ± 1952 pg/mL was observed at 0.41 ± 0.21 hours. The extent of absorption of the tablet, based upon methylergonovine plasma concentrations, was found to be equivalent to that of the I.M. solution given orally, and the extent of oral absorption of the I.M. solution was proportional to the dose following administration of 0.1, 0.2, and 0.4 mg. When given intramuscularly, the extent of absorption of Methergine solution was about 25% greater than the tablet. The volume of distribution (Vdss/F) of methylergonovine was calculated to be 56.1 ± 17.0 liters, and the plasma clearance (CLp/F) was calculated to be 14.4 ± 4.5 liters per hour. The plasma level decline was biphasic with a mean elimination half-life of 3.39 hours (range 1.5 to 12.7 hours). A delayed gastrointestinal absorption (Tmax about 3 hours) of Methergine tablet might be observed in postpartum women during continuous treatment with this oxytocic agent.

INDICATIONS AND USAGE

For routine management after delivery of the placenta; postpartum atony and hemorrhage; subinvolution. Under full obstetric supervision, it may be given in the second stage of labor following delivery of the anterior shoulder.

CONTRAINDICATIONS

Hypertension; toxemia; pregnancy; and hypersensitivity.

WARNINGS

This drug should not be administered I.V. routinely because of the possibility of inducing sudden hypertensive and cerebrovascular accidents. If I.V. administration is considered essential as a lifesaving measure, Methergine® (methylergonovine maleate) should be given slowly over a period of no less than 60 seconds with careful monitoring of blood pressure. Intra-arterial or periarterial injection should be strictly avoided.

PRECAUTIONS

General

Caution should be exercised in the presence of sepsis, obliterative vascular disease, hepatic or renal involvement. Also use with caution during the second stage of labor. The necessity for manual removal of a retained placenta should occur only rarely with proper technique and adequate allowance of time for its spontaneous separation.

Drug Interactions

CYP 3A4 Inhibitors (e.g., Macrolide Antibiotics and Protease Inhibitors)

There have been rare reports of serious adverse events in connection with the coadministration of certain ergot alkaloid drugs (e.g., dihydroergotamine and ergotamine) and potent CYP 3A4 inhibitors, resulting in vasospasm leading to cerebral ischemia and/or ischemia of the extremities. Although there have been no reports of such interactions with methylergonovine alone, potent CYP 3A4 inhibitors should not be coadministered with methylergonovine. Examples of some of the more potent CYP 3A4 inhibitors include macrolide antibiotics (e.g., erythromycin, troleandomycin, clarithromycin), HIV protease or reverse transcriptase inhibitors (e.g., ritonavir, indinavir, nelfinavir, delavirdine) or azole antifungals (e.g., ketoconazole, itraconazole, voriconazole). Less potent CYP 3A4 inhibitors should be administered with caution. Less potent inhibitors include saquinavir, nefazodone, fluconazole, grapefruit juice, fluoxetine, fluvoxamine, zileuton, and clotrimazole. These lists are not exhaustive, and the prescriber should consider the effects on CYP 3A4 of other agents being considered for concomitant use with methylergonovine.

No pharmacokinetic interactions involving other cytochrome P450 isoenzymes are known.

Caution should be exercised when Methergine® (methylergonovine maleate) is used concurrently with other vasoconstrictors or ergot alkaloids.

Carcinogenesis, Mutagenesis, Impairment of Fertility

No long-term studies have been performed in animals to evaluate carcinogenic potential. The effect of the drug on mutagenesis or fertility has not been determined.

Pregnancy

Category C. Animal reproductive studies have not been conducted with Methergine. It is also not known whether methylergonovine maleate can cause fetal harm or can affect reproductive capacity. Use of Methergine is contraindicated during pregnancy because of its uterotonic effects. (See INDICATIONS AND USAGE.)

Labor and Delivery

The uterotonic effect of Methergine is utilized after delivery to assist involution and decrease hemorrhage, shortening the third stage of labor.

Nursing Mothers

Methergine® (methylergonovine maleate) may be administered orally for a maximum of 1 week postpartum to control uterine bleeding. Recommended dosage is 1 tablet (0.2 mg) 3 or 4 times daily. At this dosage level a small quantity of drug appears in mothers’ milk. Caution should be exercised when Methergine is administered to a nursing woman.

Pediatric Use

Safety and effectiveness in pediatric patients have not been established.

Geriatric Use

Clinical studies of Methergine did not include sufficient number of subjects aged 65 and over to determine whether they respond differently from younger subjects. Other reported clinical experience has not identified differences in response between the elderly and younger patients. In general dose selection for an elderly patient should be cautious, usually starting at the low end of the dosing range, reflecting the greater frequency of decreased hepatic, renal, or cardiac function, and of concomitant disease or other drug therapy.

ADVERSE REACTIONS

The most common adverse reaction is hypertension associated in several cases with seizure and/or headache. Hypotension has also been reported. Nausea and vomiting have occurred occasionally. Rarely observed reactions have included: acute myocardial infarction, transient chest pains, arterial spasm (coronary and peripheral), bradycardia, tachycardia, dyspnea, hematuria, thrombophlebitis, water intoxication, hallucinations, leg cramps, dizziness, tinnitus, nasal congestion, diarrhea, diaphoresis, palpitation, rash, and foul taste.^1

There have been rare isolated reports of anaphylaxis, without a proven causal relationship to the drug product.

DRUG ABUSE AND DEPENDENCE

Methergine® (methylergonovine maleate) has not been associated with drug abuse or dependence of either a physical or psychological nature.

OVERDOSAGE

Symptoms of acute overdose may include: nausea, vomiting, abdominal pain, numbness, tingling of the extremities, rise in blood pressure, in severe cases followed by hypotension, respiratory depression, hypothermia, convulsions, and coma.

Because reports of overdosage with Methergine® (methylergonovine maleate) are infrequent, the lethal dose in humans has not been established. The oral LD50 (in mg/kg) for the mouse is 187, the rat 93, and the rabbit 4.5.^2 Several cases of accidental Methergine injection in newborn infants have been reported, and in such cases 0.2 mg represents an overdose of great magnitude. However, recovery occurred in all but one case following a period of respiratory depression, hypothermia, hypertonicity with jerking movements, and, in one case, a single convulsion.

Also, several children 1-3 years of age have accidentally ingested up to 10 tablets (2 mg) with no apparent ill effects. A postpartum patient took 4 tablets at one time in error and reported paresthesias and clamminess as her only symptoms.

Treatment of acute overdosage is symptomatic and includes the usual procedures of:

1. removal of offending drug by inducing emesis, gastric lavage, catharsis, and supportive diuresis.
2. maintenance of adequate pulmonary ventilation, especially if convulsions or coma develop.
3. correction of hypotension with pressor drugs as needed.
4. control of convulsions with standard anticonvulsant agents.
5. control of peripheral vasospasm with warmth to the extremities if needed.^3

DOSAGE AND ADMINISTRATION

Parenteral drug products should be inspected visually for particulate matter and discoloration prior to administration.

Intramuscularly

1 mL, 0.2 mg, after delivery of the anterior shoulder, after delivery of the placenta, or during the puerperium. May be repeated as required, at intervals of 2-4 hours.

Intravenously

Dosage same as intramuscular. (See WARNINGS.)

Orally

One tablet, 0.2 mg, 3 or 4 times daily in the puerperium for a maximum of 1 week.

HOW SUPPLIED

Tablets

0.2 mg round, coated, orchid, branded “78-54” one side, “SANDOZ” other side.

Bottles of 100…………………………………………………………..NDC 0078-0054-05

Ampuls

1 mL size

Boxes of 20…………………………………………………………….NDC 0078-0053-03

Store and Dispense

Tablets: Store below 25°C (77°F); in tight, light-resistant container.

Ampuls: Store in refrigerator, 2ºC-8°C (36°F-46°F). Protect from light. Administer only if solution is clear and colorless.

REFERENCES

1. Information on Adverse Reactions supplied by Medical Services Department, Novartis Pharmaceuticals, E. Hanover, N.J., based on computerized clinical reports.
2. Berde, B. and Schild, H.O.: Ergot Alkaloids and Related Compounds, Springer-Verlag, New York, 1978, p. 810.
3. Treatment of Acute Overdosage. Novartis Consumer Health, Inc. Rx Products. Novartis, Medical Services Department.

T2006-91

REV: OCTOBER 2006 Printed in the U.S.A. 5000981

5000982

Distributed by:

Novartis Pharmaceuticals Corporation

East Hanover, New Jersey 07936

© Novartis

PRINCIPAL DISPLAY PANEL

NDC 66336-0402-XX
NDC 66336-0402-44

Package Label – 0.2 mg Tablets

Rx Only

Methergine® (methylergonovine maleate) Tablets, USP

4 Tablets